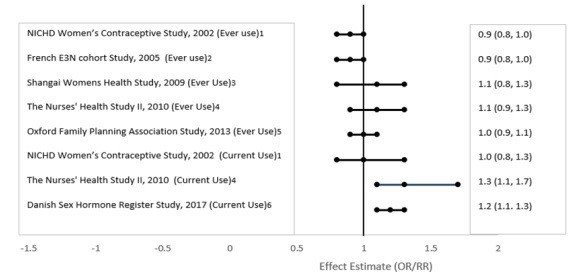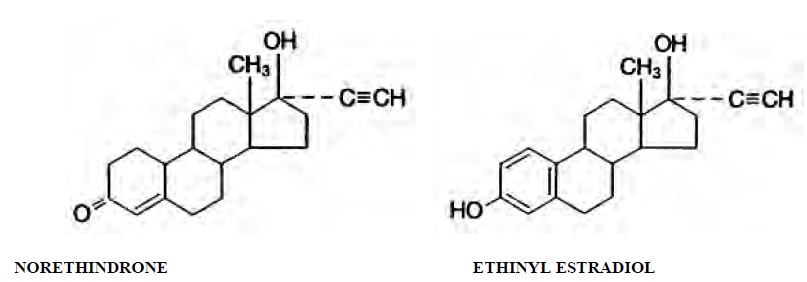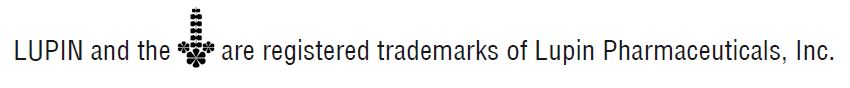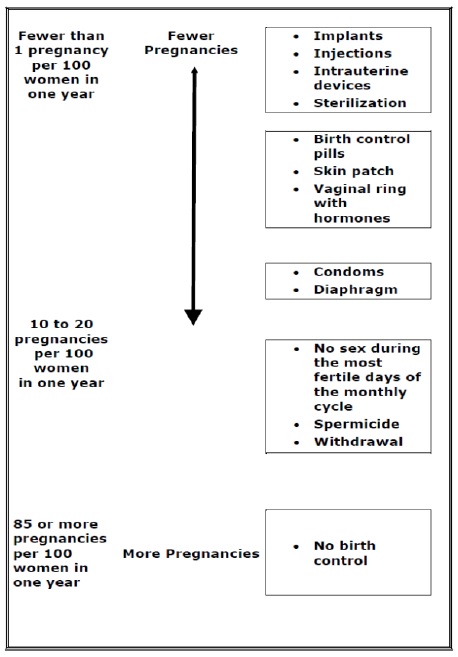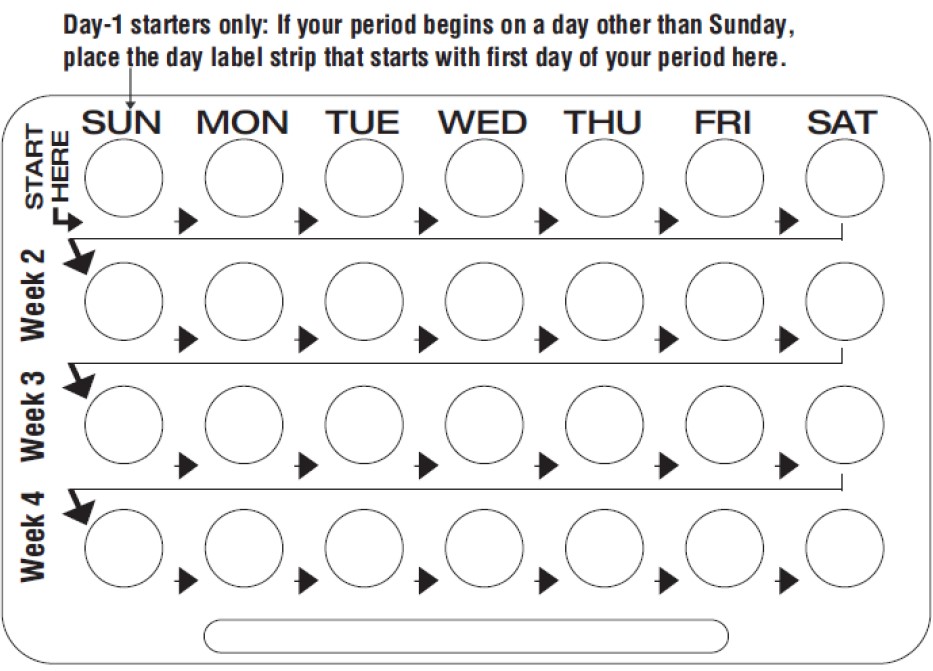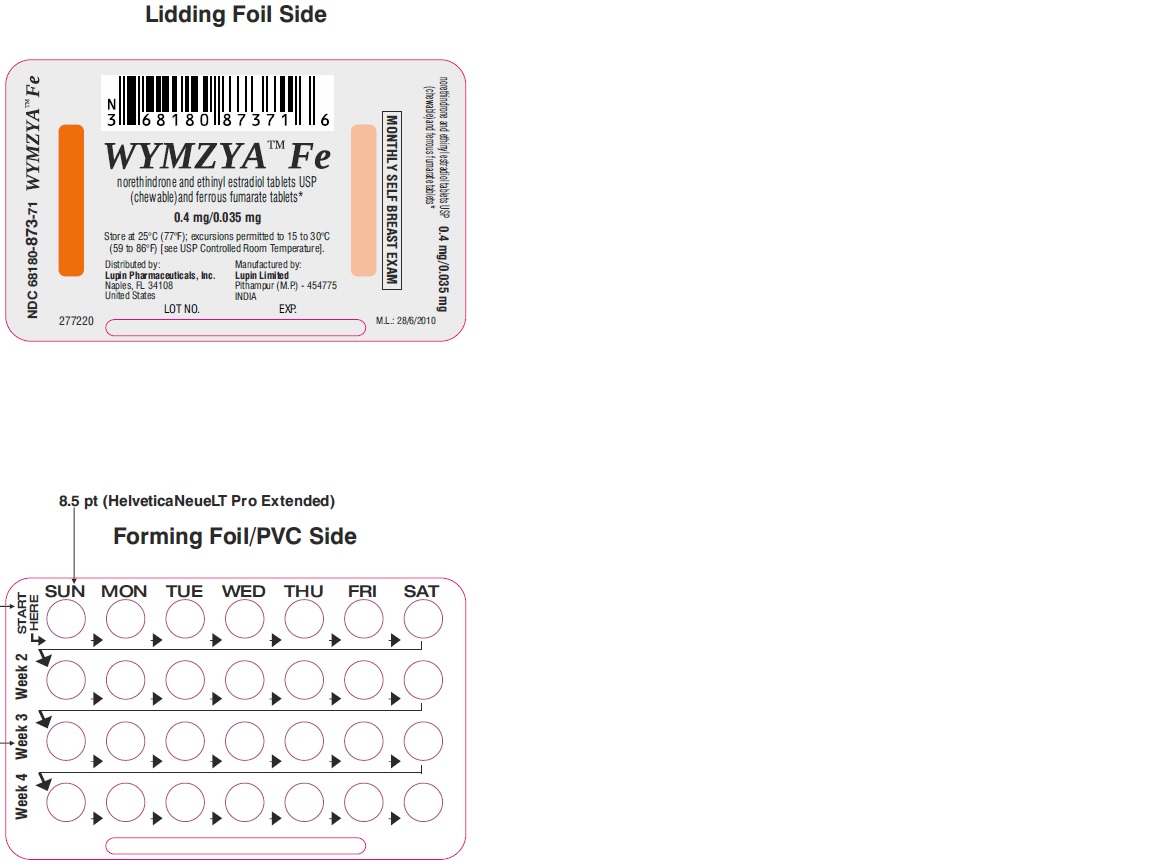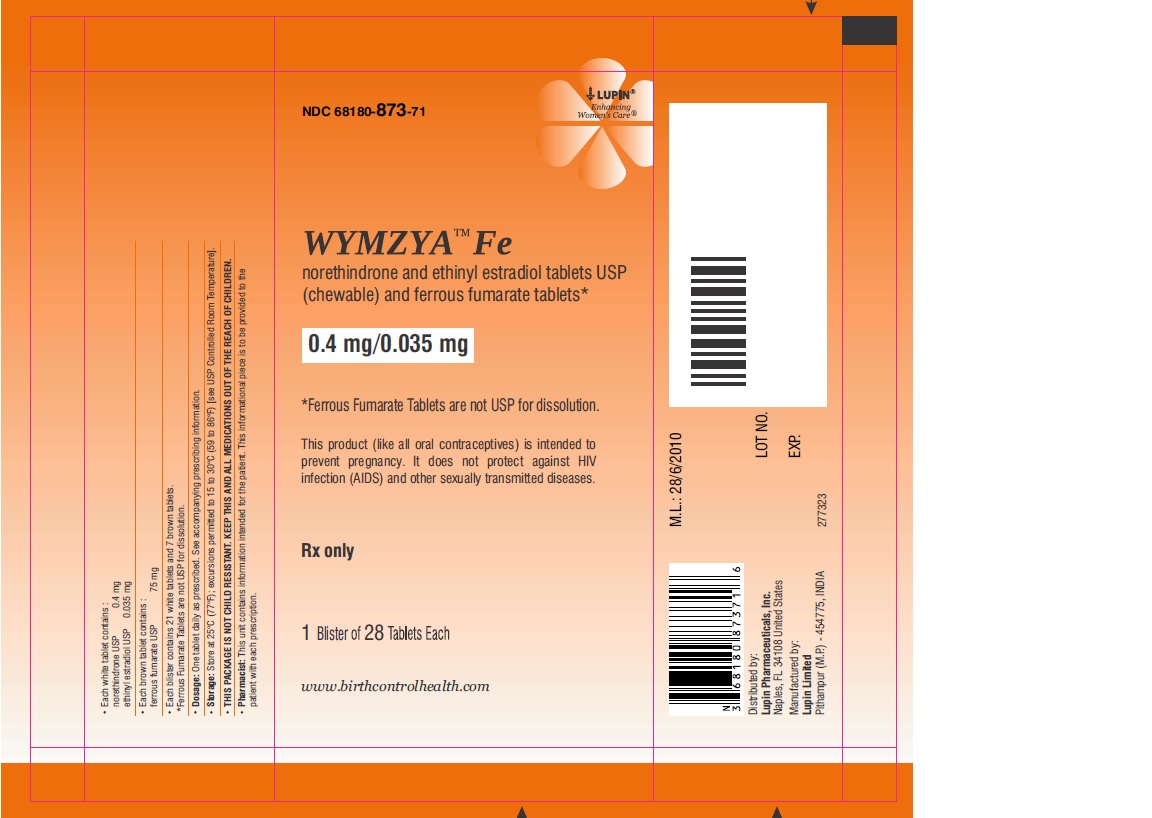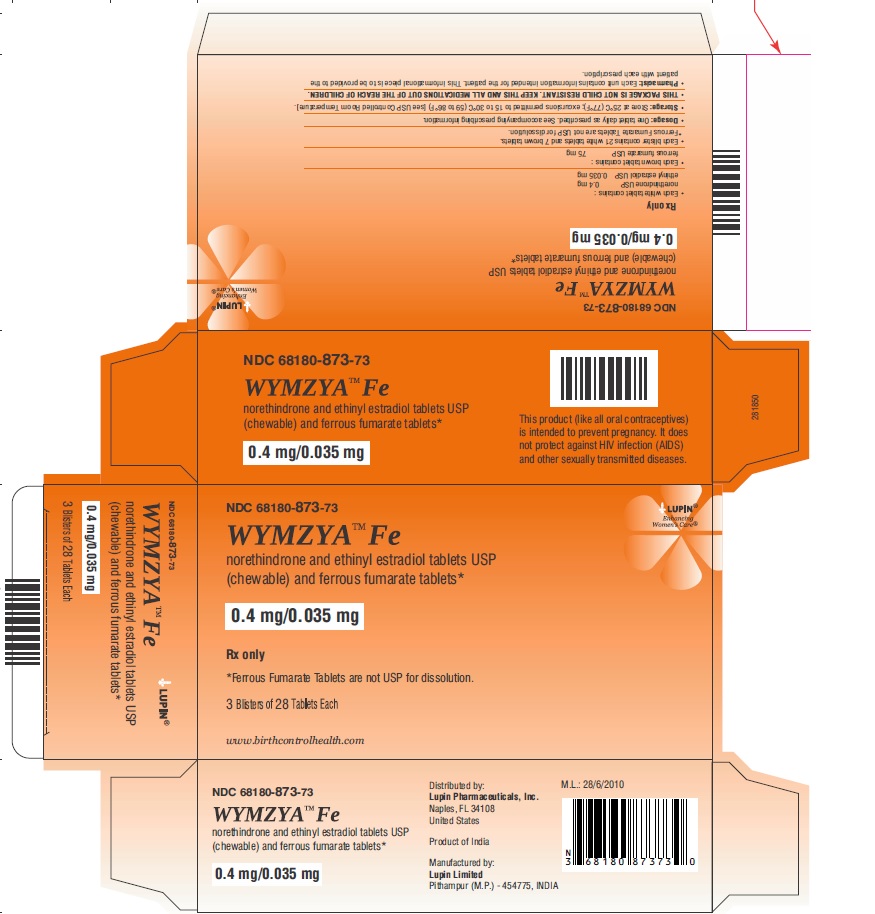 DRUG LABEL: WYMZYA Fe

NDC: 68180-873 | Form: KIT | Route: ORAL
Manufacturer: Lupin Pharmaceuticals, Inc.
Category: prescription | Type: HUMAN PRESCRIPTION DRUG LABEL
Date: 20251119

ACTIVE INGREDIENTS: NORETHINDRONE 0.4 mg/1 1; ETHINYL ESTRADIOL 0.035 mg/1 1
INACTIVE INGREDIENTS: .ALPHA.-TOCOPHEROL; ANHYDROUS LACTOSE; CELLULOSE, MICROCRYSTALLINE; MAGNESIUM STEARATE; MANNITOL; POVIDONE K30; SODIUM STARCH GLYCOLATE TYPE A POTATO; SUCRALOSE; VANILLIN; CELLULOSE, MICROCRYSTALLINE; FERROUS FUMARATE; MAGNESIUM STEARATE; POVIDONE K30; SODIUM STARCH GLYCOLATE TYPE A POTATO; SUCROSE

HIGHLIGHTS OF PRESCRIBING INFORMATION

These highlights do not include all the information needed to use WYMZYA Fe safely and effectively. See Full Prescribing Information for WYMZYA Fe.
WYMZYA Fe [norethindrone and ethinyl estradiol tablets (chewable) and ferrous fumarate tablets] for oral use
Initial U.S. Approval: 1975

RECENT MAJOR CHANGES

Warnings and Precautions (5.11) 12/2021

BOXED WARNING

WARNING: CIGARETTE SMOKING AND SERIOUS CARDIOVASCULAR EVENTS

See Full Prescribing Information for complete boxed warning.

- WYMZYA Fe is contraindicated in women over 35 years old who smoke. (4)
- Cigarette smoking increases the risk of serious cardiovascular events from combination oral contraceptives (COC) use. (4)

1 INDICATIONS AND USAGE

- WYMZYA Fe is a progestin/estrogen COC indicated for use by females of reproductive potential to prevent pregnancy. (1)

2 DOSAGE AND ADMINISTRATION

- Take one tablet by mouth at the same time every day. Tablets may be chewed or swallowed. (2.1)
- Take tablets in the order directed on the blister .(2.1)

3 DOSAGE FORMS AND STRENGTHS

WYMZYA Fe consists of 28 tablets in the following order (3):

- 21 white tablets (active), each containing 0.4 mg norethindrone and 35 mcg ethinyl estradiol
- 7 brown tablets (non-hormonal placebo), each containing 75 mg ferrous fumarate. The ferrous fumarate tablets do not serve any therapeutic purpose.

4 CONTRAINDICATIONS

- A high risk of arterial or venous thrombotic diseases (4)
- Liver tumors or liver disease (4)
- Undiagnosed abnormal uterine bleeding (4)
- Pregnancy (4)
- Current diagnosis of, or history of, breast cancer, which may be hormone-sensitive (4)
- Co-administration with Hepatitis C drug combinations containing ombitasvir/paritaprevir/ritonavir, with or without dasabuvir (4)

5 WARNINGS AND PRECAUTIONS

- Thrombotic Disorders and Other Vascular Problems: Stop WYMZYA Fe if a thrombotic event occurs. Stop at least 4 weeks before through 2 weeks after major surgery. Start no earlier than 4 weeks after delivery, in women who are not breastfeeding (5.1)
- Liver disease : Discontinue WYMZYA Fe if jaundice occurs (5.2)
- High blood pressure : If used in women with well-controlled hypertension, monitor blood pressure and stop WYMZYA Fe if blood pressure rises significantly. (5.4)
- Carbohydrate and lipid metabolic effects : Monitor prediabetic and diabetic women taking WYMZYA Fe. Consider an alternative contraceptive method for women with uncontrolled dyslipidemia (5.6)
- Headache : Evaluate significant change in headaches and discontinue WYMZYA Fe if indicated (5.7)
- Bleeding Irregularities and Amenorrhea : Evaluate irregular bleeding or amenorrhea (5.8)

6 ADVERSE REACTIONS

The most common adverse reactions were: irregular uterine bleeding, nausea, breast tenderness, and headache. (6)

To report SUSPECTED ADVERSE REACTIONS, contact Lupin Pharmaceuticals, Inc. at 1-800-399-2561 or FDA at 1-800-FDA-1088 or www.fda.gov/medwatch.

7 DRUG INTERACTIONS

- Drugs or herbal products that induce certain enzymes, including CYP3A4, may decrease the effectiveness of COCs or increase breakthrough bleeding. Counsel patients to use a back-up method or alternative method of contraception when enzyme inducers are used with COCs (7.1)

8 USE IN SPECIFIC POPULATIONS

- Nursing mothers: Advise use of another contraceptive method.

WYMZYA Fe can decrease milk production. (8.3)

FULL PRESCRIBING INFORMATION

BOXED WARNING

WARNING: CIGARETTE SMOKING AND SERIOUS CARDIOVASCULAR EVENTS Cigarette smoking increases the risk of serious cardiovascular events from combination oral contraceptive (COC) use. This risk increases with age, particularly in women over 35 years of age, and with the number of cigarettes smoked. For this reason, COCs are contraindicated in women who are over 35 years of age and smoke [see CONTRAINDICATIONS (4)].

1 INDICATIONS AND USAGE

WYMZYATM Fe is indicated for use by females of reproductive potential to prevent pregnancy.

2 DOSAGE AND ADMINISTRATION

2.1 How to Start WYMZYA Fe

WYMZYA Fe is dispensed in a blister [see HOW SUPPLIED/STORAGE AND HANDLING (16)]. WYMZYA Fe may be started using either a Day 1 start or a Sunday start (see Table 1). For the first cycle of a Sunday Start regimen, an additional method of contraception should be used until after the first 7 consecutive days of administration.

2.2 How to Take WYMZYA Fe

WYMZYA Fe (white active tablets and brown placebo tablets) may be swallowed whole or chewed and swallowed. If the tablet is chewed, the patient should drink a full glass (8 ounces) of liquid immediately after swallowing.

Table 1: Instructions for Administration of WYMZYA Fe
Starting CHCs in women not currently using hormonal contraception (Day 1 Start or Sunday Start) Important: Consider the possibility of ovulation and conception prior to initiation of this product. Tablet Color: ● WYMZYA Fe active tablets are white (Day 1 to Day 21). ● WYMZYA Fe placebo tablets are brown (Day 22 to Day 28). | Day 1 Start: ● Take first white active tablet on the first day of menses. ● Take subsequent white active tablets once daily at the same time each day for a total of 21 days. ● Take one brown placebo tablet daily for 7 days and at the same time of day that active tablets were taken. ● Begin each subsequent pack on the same day of the week as the first cycle pack (i.e., on the day after taking the last inactive tablet).
 | Sunday Start: ● Take first active tablet on the first Sunday after the onset of menses. Due to the potential risk of becoming pregnant, use additional non-hormonal contraception (such as condoms and spermicide) for the first seven days of the patient's first cycle pack of WYMZYA Fe . ● Take subsequent white active tablets once daily at the same time each day for a total of 21 days. ● Take one brown placebo tablet daily for the following 7 days and at the same time of day that active tablets were taken. ● Begin each subsequent pack on the same day of the week as the first cycle pack (i.e., on the Sunday after taking the last inactive tablet) and additional non-hormonal contraceptive is not needed.
Switching to WYMZYA Fe from another hormonal contraceptive | Start on the same day that a new pack of the previous hormonal contraceptive would have started.
Switching from another contraceptive method to WYMZYA Fe | Start WYMZYA Fe :
● Transdermal patch | ● On the day when next application would have been scheduled
● Vaginal ring | ● On the day when next insertion would have been scheduled
● Injection | ● On the day when next injection would have been scheduled
● Intrauterine contraceptive | ● On the day of removal ● If the IUD is not removed on first day of the patient's menstrual cycle, additional non-hormonal contraceptive (such as condoms and spermicide) is needed for the first seven days of the first cycle pack.
● Implant | ● On the day of removal
Complete instructions to facilitate patient counseling on proper tablet usage are located in the FDA-Approved Patient Labeling.

Starting WYMZYA Fe after Abortion or Miscarriage

First-trimester:

- After a first-trimester abortion or miscarriage, WYMZYA Fe may be started immediately. An additional method of contraception is not needed if WYMZYA Fe is started within 5 days after termination of the pregnancy.
- If WYMZYA Fe is not started within 5 days after termination of the pregnancy, the patient should use additional non-hormonal contraception (such as condoms and spermicide) for the first seven days of her first cycle pack of WYMZYA Fe.

Second-trimester:

- Do not start until 4 weeks after a second-trimester abortion or miscarriage, due to the increased risk of thromboembolic disease. Start WYMZYA Fe, following the instructions in Table 1 for Day 1 or Sunday start, as desired. If using Sunday start, use additional non- hormonal contraception (such as condoms and spermicide) for the first seven days of the patient's first cycle pack of WYMZYA Fe. [see CONTRAINDICATIONS (4), WARNINGS AND PRECAUTIONS (5.1), and FDA-APPROVED PATIENT LABELING.]

Starting WYMZYA Fe after Childbirth

- Do not start until 4 weeks after delivery, due to the increased risk of thromboembolic disease. Start contraceptive therapy with WYMZYA Fe following the instructions in Table 1 for women not currently using hormonal contraception.
- If the woman has not yet had a period postpartum, consider the possibility of ovulation and conception occurring prior to use of WYMZYA Fe. [see CONTRAINDICATIONS (4), WARNINGS AND PRECAUTIONS (5.1), USE IN SPECIFIC POPULATIONS (8.1 and 8.3), and FDA-APPROVED PATIENT LABELING] .

2.3 Missed Tablets

Table 2: Instructions for Missed WYMZYA Fe Tablets
● If one white active tablet is missed in Weeks 1, 2, or 3 | Take the tablet as soon as possible. Continue taking one tablet a day until the pack is finished.
● If two white active tablets are missed in Week 1 or Week 2 | Take the two missed tablets as soon as possible and the next two active tablets the next day. Continue taking one tablet a day until the pack is finished. Additional non-hormonal contraception (such as condoms and spermicide) should be used as back-up if the patient has sex within 7 days after missing tablets.
● If two white active tablets are missed in Week 3 or three or more white active tablets are missed in a row in Weeks 1, 2, or 3 | Day 1 start : Throw out the rest of the pack and start a new pack that same day. Sunday start : Continue taking one tablet a day until Sunday, then throw out the rest of the pack and start a new pack that same day. Additional non-hormonal contraception (such as condoms and spermicide) should be used as back-up if the patient has sex within 7 days after missing tablets.

2.4 Advice in Case of Gastrointestinal Disturbances

In case of severe vomiting or diarrhea, absorption may not be complete and additional contraceptive measures should be taken. If vomiting or diarrhea occurs within 3 to 4 hours after taking an active tablet, handle this as a missed tablet [see FDA-APPROVED PATIENT LABELING].

3 DOSAGE FORMS AND STRENGTHS

WYMZYA Fe [norethindrone and ethinyl estradiol tablets USP (chewable) and ferrous fumarate tablets] is available in blister.

Each blister contains 28 tablets in the following order:

- 21 white to off-white, round (active), flat face, beveled edge tablets debossed with "LU" on one side and "M21" on the other side and each containing 0.4 mg norethindrone and 35 mcg ethinyl estradiol.
- 7 brown, mottled, round (non-hormonal placebo), flat face, beveled edge tablets debossed with "LU" on one side and "M22" on the other side and each containing 75 mg ferrous fumarate. The ferrous fumarate tablets do not serve any therapeutic purpose.

4 CONTRAINDICATIONS

WYMZYA Fe is contraindicated in females who are known to have or develop the following conditions:

- A high risk of arterial or venous thrombotic diseases. Examples include women who are known to:
  - Smoke, if over age 35 [see BOXED WARNING and WARNINGS AND PRECAUTIONS (5.1)]
  - Have deep vein thrombosis or pulmonary embolism, now or in the past [see WARNINGS AND PRECAUTIONS (5.1)]
  - Have inherited or acquired hypercoagulopathies [see WARNINGS AND PRECAUTIONS (5.1)]
  - Have cerebrovascular disease [see WARNINGS AND PRECAUTIONS (5.1)]
  - Have coronary artery disease [see WARNINGS AND PRECAUTIONS (5.1)]
  - Have thrombogenic valvular or thrombogenic rhythm diseases of the heart (for example, subacute bacterial endocarditis with valvular disease, or atrial fibrillation) [see WARNINGS AND PRECAUTIONS (5.1)]
  - Have uncontrolled hypertension [see WARNINGS AND PRECAUTIONS (5.4)]
  - Have diabetes mellitus with vascular disease [see WARNINGS AND PRECAUTIONS (5.6)]
  - Have headaches with focal neurological symptoms or have migraine headaches with aura [see WARNINGS AND PRECAUTIONS (5.7)]

5 WARNINGS AND PRECAUTIONS

5.1 Thrombotic Disorders and Other Vascular Problems

- Stop WYMZYA Fe if an arterial thrombotic event or venous thromboembolic (VTE) event occurs.
- Stop WYMZYA Fe if there is unexplained loss of vision, proptosis, diplopia, papilledema, or retinal vascular lesions. Evaluate for retinal vein thrombosis immediately.
- If feasible, stop WYMZYA Fe at least 4 weeks before and through 2 weeks after major surgery or other surgeries known to have an elevated risk of VTE as well as during the following prolonged immobilization.
- Start WYMZYA Fe no earlier than 4 weeks after delivery, in women who are not breastfeeding. The risk of postpartum VTE decreases after the third postpartum week, whereas the risk of ovulation increases after the third postpartum week.
- The use of COCs increases the risk of VTE. However, pregnancy increases the risk of VTE as much or more than the use of COCs. The risk of VTE in women using COCs is 3 to 9 per 10,000 woman-years. The risk of VTE is highest during the first year of use of COCs and when restarting hormonal contraception after a break of 4 weeks or longer. The risk of thromboembolic disease due to COCs gradually disappears after use is discontinued.
- Use of COCs also increases the risk of arterial thromboses such as strokes and myocardial infarctions, especially in women with other risk factors for these events. COCs have been shown to increase both the relative and attributable risks of cerebrovascular events (thrombotic and hemorrhagic strokes). The risk increases with age, particularly in women over 35 years of age who smoke.
- Use COCs with caution in women with cardiovascular disease risk factors.

5.2 Liver Disease

Impaired Liver Function

Do not use WYMZYA Fe in women with liver disease, such as acute viral hepatitis or severe (decompensated) cirrhosis of liver [see CONTRAINDICATIONS (4)]. Acute or chronic disturbances of liver function may necessitate the discontinuation of COC use until markers of liver function return to normal and COC causation has been excluded. Discontinue WYMZYA Fe if jaundice develops.

Liver Tumors

WYMZYA Fe is contraindicated in women with benign and malignant liver tumors [see CONTRAINDICATIONS (4)]. Hepatic adenomas are associated with COC use. An estimate of the attributable risk is 3.3 cases/100,000 COC users. Rupture of hepatic adenomas may cause death through intra-abdominal hemorrhage.

Studies have shown an increased risk of developing hepatocellular carcinoma in long-term (>8 years) COC users. However, the risk of liver cancers in COC users is less than one case per million users.

5.3 Risk of Liver Enzyme Elevations with Concomitant Hepatitis C Treatment

During clinical trials with the Hepatitis C combination drug regimen that contains ombitasvir/paritaprevir/ritonavir, with or without dasabuvir, ALT elevations greater than 5 times the upper limit of normal (ULN),including some cases greater than 20 times the ULN, were significantly more frequent in women using ethinyl estradiol-containing medications, such as COCs. Discontinue WYMZYA Fe prior to starting therapy with the combination drug regimen ombitasvir/paritaprevir/ritonavir, with or without dasabuvir [see CONTRAINDICATIONS (4)].

WYMZYA Fe can be restarted approximately 2 weeks following completion of treatment with the Hepatitis C combination drug regimen.

5.4 High Blood Pressure

WYMZYA Fe is contraindicated in women with uncontrolled hypertension or hypertension with vascular disease [see CONTRAINDICATIONS (4)]. For women with well-controlled hypertension, monitor blood pressure and stop WYMZYA Fe if blood pressure rises significantly.

An increase in blood pressure has been reported in women taking COCs, and this increase is more likely in older women with extended duration of use. The incidence of hypertension increases with increasing concentrations of progestin.

5.5 Gallbladder Disease

Studies suggest a small increased relative risk of developing gallbladder disease among COC users. Use of COCs may worsen existing gallbladder disease. A past history of COC-related cholestasis predicts an increased risk with subsequent COC use. Women with a history of pregnancy-related cholestasis may be at an increased risk for COC related cholestasis.

5.6 Carbohydrate and Lipid Metabolic Effects

Carefully monitor prediabetic and diabetic women who take WYMZYA Fe. COCs may decrease glucose tolerance.

Consider alternative contraception for women with uncontrolled dyslipidemia. A small proportion of women will have adverse lipid changes while on COCs.

Women with hypertriglyceridemia, or a family history thereof, may be at an increased risk of pancreatitis when using COCs.

5.7 Headache

If a woman taking WYMZYA Fe develops new headaches that are recurrent, persistent, or severe, evaluate the cause and discontinue WYMZYA Fe if indicated.

Consider discontinuation of WYMZYA Fe in the case of increased frequency or severity of migraine during COC use (which may be prodromal of a cerebrovascular event).

5.8 Bleeding Irregularities and Amenorrhea

Unscheduled Bleeding and Spotting

Unscheduled (breakthrough or intracyclic) bleeding and spotting sometimes occur in patients on COCs, especially during the first three months of use. If bleeding persists or occurs after previously regular cycles, check for causes such as pregnancy or malignancy. If pathology and pregnancy are excluded, bleeding irregularities may resolve over time or with a change to a different contraceptive product.

Amenorrhea and Oligomenorrhea

Women who use WYMZYA Fe may experience amenorrhea. Some women may experience amenorrhea or oligomenorrhea after discontinuation of COCs, especially when such a condition was preexistent.

If scheduled (withdrawal) bleeding does not occur, consider the possibility of pregnancy. If the patient has not adhered to the prescribed dosing schedule (missed one or more active tablets or started taking them on a day later than she should have), consider the possibility of pregnancy at the time of the first missed period and take appropriate diagnostic measures. If the patient has adhered to the prescribed regimen and misses two consecutive periods, rule out pregnancy.

5.9 COC Use Before or During Early Pregnancy

Extensive epidemiologic studies have revealed no increased risk of birth defects in women who have used oral contraceptives prior to pregnancy. Studies also do not suggest a teratogenic effect, particularly in so far as cardiac anomalies and limb reduction defects are concerned, when oral contraceptives are taken inadvertently during early pregnancy. Discontinue WYMZYA Fe use if pregnancy is confirmed.

Administration of COCs to induce withdrawal bleeding should not be used as a test for pregnancy [see USE IN SPECIFIC POPULATIONS (8.1)].

5.10 Depression

Carefully observe women with a history of depression and discontinue WYMZYA Fe if depression recurs to a serious degree.

5.11 Malignant Neoplasms

Breast Cancer
WYMZYA Fe is contraindicated in females who currently have or have had breast cancer because breast cancer may be hormonally sensitive [see CONTRAINDICATIONS (4)].
Epidemiology studies have not found a consistent association between use of combined oral contraceptives (COCs) and breast cancer risk. Studies do not show an association between ever (current or past) use of COCs and risk of breast cancer. However, some studies report a small increase in the risk of breast cancer among current or recent users (<6 months since last use) and current users with longer duration of COC use [see POSTMARKETING EXPERIENCE (6.2)].
Cervical Cancer
Some studies suggest that COC use has been associated with an increase in the risk of cervical cancer or intraepithelial neoplasia. However, there continues to be controversy about the extent to which such findings may be due to differences in sexual behavior and other factors.

5.12 Effect on Binding Globulins

The estrogen component of COCs may raise the serum concentrations of thyroxine-binding globulin, sec hormone-binding globulin, and cortisol-binding globulin. The dose of replacement thyroid hormone or cortisol therapy may need to be increased.

5.13 Monitoring

A woman who is taking COCs should have a yearly visit with her healthcare provider for a blood pressure check and for other indicated healthcare.

5.14 Hereditary Angioedema

In women with hereditary angioedema, exogenous estrogens may induce or exacerbate symptoms of angioedema.

5.15 Chloasma

Chloasma may occasionally occur, especially in women with a history of chloasma gravidarum. Women with a tendency to chloasma should avoid exposure to the sun or ultraviolet radiation while taking WYMZYA Fe.

6 ADVERSE REACTIONS

6.2 Postmarketing Experience

Five studies that compared breast cancer risk between ever-users (current or past use) of COCs and never-users of COCs reported no association between ever use of COCs and breast cancer risk, with effect estimates ranging from 0.90 - 1.12 (Figure 1).

Three studies compared breast cancer risk between current or recent COC users (<6 months since last use) and never users of COCs (Figure 1). One of these studies reported no association between breast cancer risk and COC use. The other two studies found an increased relative risk of 1.19 - 1.33 with current or recent use. Both of these studies found an increased risk of breast cancer with current use of longer duration, with relative risks ranging from 1.03 with less than one year of COC use to approximately 1.4 with more than 8-10 years of COC use.

Figure 1: Risk of Breast Cancer with Combined Oral Contraceptive Use

RR = relative risk; OR = odds ratio; HR = hazard ratio. "ever COC" are females with current or past COC use; "never COC use" are females that never used COCs.

The following serious adverse reactions with the use of COCs are discussed elsewhere in the labeling:

- Serious cardiovascular events and stroke [see BOXED WARNING and WARNINGS AND PRECAUTIONS (5.1)]
- Vascular events [see WARNINGS AND PRECAUTIONS (5.1)]
- Liver disease [see WARNINGS AND PRECAUTIONS (5.2)]

The following adverse reactions are commonly reported by COC users. Because these reactions are voluntarily reported by from a population of uncertain size, it is not always possible to reliably estimate their frequency or establish a causal relationship to drug exposure:

- Irregular uterine bleeding
- Nausea
- Breast tenderness
- Headache

7 DRUG INTERACTIONS

Consult the labeling of concurrently used drugs to obtain further information about interactions with hormonal contraceptives or the potential for enzyme alterations.

7.1 Effects of Other Drugs on Combined Oral Contraceptives

Substances Decreasing the Plasma Concentrations of COCs and Potentially Diminishing the Efficacy of COCs

Drugs or herbal products that induce certain enzymes, including cytochrome P450 3A4 (CYP3A4), may decrease the plasma concentrations of COCs and potentially diminish the effectiveness of COCs or increase breakthrough bleeding. Some drugs or herbal products that may decrease the effectiveness of hormonal contraceptives include phenytoin, barbiturates, carbamazepine, bosentan, felbamate, griseofulvin, oxcarbazepine, rifampicin, topiramate, rifabutin, rufinamide, aprepitant, and products containing St. John's wort. Interactions between hormonal contraceptives and other drugs may lead to breakthrough bleeding and/or contraceptive failure. Counsel women to use an alternative method of contraception or a back-up method when enzyme inducers are used with COCs, and to continue back-up contraception for 28 days after discontinuing the enzyme inducer to ensure contraceptive reliability.

Colesevelam

Colesevelam, a bile acid sequestrant, given together with a COC, has been shown to significantly decrease the AUC of EE. The drug interaction between the contraceptive and colesevelam was decreased when the two drug products were given 4 hours apart.

Substances Increasing the Plasma Concentrations of COCs

Co-administration of atorvastatin or rosuvastatin and certain COCs containing EE increase AUC values for EE by approximately 20 to 25%. Ascorbic acid and acetaminophen may increase plasma EE concentrations, possibly by inhibition of conjugation. CYP3A4 inhibitors, such as itraconazole, fluconazole, grapefruit juice, or ketoconazole may increase plasma hormone concentrations.

Human Immunodeficiency Virus (HIV)/Hepatitis C Virus (HCV) Protease Inhibitors and Non- nucleoside Reverse Transcriptase Inhibitors

Significant changes (increase or decrease) in the plasma concentrations of estrogen and/or progestin have been noted in some cases of co-administration with HIV protease inhibitors (decrease [e.g., nelfinavir, ritonavir, darunavir/ritonavir, (fos)amprenavir/ritonavir, lopinavir/ritonavir, and tipranavir/ritonavir] or increase [e.g., indinavir and atazanavir/ritonavir])/HCV protease inhibitors (decrease [e.g., nevirapine] or increase [e.g., etravirine]).

7.2 Effects of Combined Oral Contraceptives on Other Drugs

COCs containing EE may inhibit the metabolism of other compounds (e.g., cyclosporine prednisolone, theophylline, tizanidine, and voriconazole) and increase their plasma concentrations. COCs have been shown to decrease plasma concentrations of acetaminophen, clofibric acid, morphine, salicylic acid, temazepam and lamotrigine. Significant decrease in plasma concentration of lamotrigine has been shown, likely due to induction of lamotrigine glucuronidation. This may reduce seizure control; therefore, dosage adjustments of lamotrigine may be necessary.

Women on thyroid hormone replacement therapy may need increased doses of thyroid hormone because the serum concentration of thyroid-binding globulin increases with use of COCs [see WARNINGS AND PRECAUTIONS (5.12)].

7.3 Concomitant Use with HCV Combination Therapy – Liver Enzyme Elevation

Do not co-administer WYMZYA Fe with HCV drug combinations containing ombitasvir/ paritaprevir/ritonavir, with or without dasabuvir, due to potential for ALT elevations [see WARNINGS AND PRECAUTIONS (5.3)].

7.4 Interference with Laboratory Tests

The use of contraceptive steroids may influence the results of certain laboratory tests, such as coagulation factors, lipids, glucose tolerance, and binding proteins.

8 USE IN SPECIFIC POPULATIONS

8.1 Pregnancy

There is little or no increased risk of birth defects in women who inadvertently use COCs during early pregnancy. Epidemiologic studies and meta-analyses have not found an increased risk of genital or non-genital birth defects (including cardiac anomalies and limb reduction defects) following exposure to low dose COCs prior to conception or during early pregnancy.

Do not use COCs to induce withdrawal bleeding as a test for pregnancy. Do not use COCs during pregnancy to treat threatened or habitual abortion.

8.3 Nursing Mothers

Advise the nursing mother to use other forms of contraception, when possible, until she has weaned her child. COCs can reduce milk production in breastfeeding mothers. This is less likely to occur once breastfeeding is well-established; however, it can occur at any time in some women. Small amounts of oral contraceptive steroids and/or metabolites are present in breast milk.

8.4 Pediatric Use

Safety and efficacy of WYMZYA Fe have been established in women of reproductive age. Efficacy is expected to be the same in post-pubertal adolescents under the age of 18 years as for users 18 years and older. Use of this product before menarche is not indicated.

8.5 Geriatric Use

WYMZYA Fe has not been studied in postmenopausal women and is not indicated in this population.

8.6 Hepatic Impairment

The pharmacokinetics of WYMZYA Fe has not been studied in women with hepatic impairment. However, steroid hormones may be poorly metabolized in patients with hepatic impairment. Acute or chronic disturbances of liver function may necessitate the discontinuation of COC use until markers of liver function return to normal and COC causation has been excluded [see CONTRAINDICATIONS (4) and WARNINGS AND PRECAUTIONS (5.2)].

8.7 Renal Impairment

The pharmacokinetics of WYMZYA Fe has not been studied in women with renal impairment.

10 OVERDOSAGE

There have been no reports of serious ill effects from overdosage of oral contraceptives, including ingestion by children. Overdosage may cause withdrawal bleeding in females and nausea.

11 DESCRIPTION

WYMZYA Fe is a combinational contraceptive containing the progestational compound norethindrone and the estrogenic compound ethinyl estradiol. The packaging includes 21 white tablets composed of norethindrone and ethinyl estradiol followed by 7 brown ferrous fumarate (placebo) tablets. The chemical name for norethindrone is 17-hydroxy-19-nor-17α-pregn-4-en-20-yn-3-one and for ethinyl estradiol the chemical name is 19-nor-17α-pregna-1,3,5(10)-trien-20-yne-3,17-diol. The structural formulas are:

The active white WYMZYA Fe tablets contain 0.4 mg norethindrone and 0.035 mg ethinyl estradiol, and the following inactive ingredients: lactose anhydrous, magnesium stearate, mannitol, microcrystalline cellulose, povidone, sodium starch glycolate, sucralose, vanillin and vitamin E.

The brown tablets contain ferrous fumarate, magnesium stearate, microcrystalline cellulose, povidone, sodium starch glycolate and sucrose. The ferrous fumarate tablets do not serve any therapeutic purpose.

FDA approved dissolution test specifications differ from USP.

12 CLINICAL PHARMACOLOGY

12.1 Mechanism of Action

COCs lower the risk of becoming pregnant primarily by suppressing ovulation. Other possible mechanisms may include cervical mucus changes that inhibit sperm penetration and endometrial changes that reduce the likelihood of implantation.

12.2 Pharmacodynamics

No specific pharmacodynamic studies were conducted with WYMZYA Fe.

12.3 Pharmacokinetics

Absorption

Ethinyl estradiol and norethindrone are rapidly absorbed with maximum plasma concentrations occurring within 2 hours after WYMZYA Fe administration (see Table 1). Norethindrone appears to be completely absorbed following oral administration; however, it is subject to first-pass metabolism resulting in an absolute bioavailability of approximately 65 percent. Large intersubject variability is reflected in a 3- to 5-fold variation in norethindrone bioavailability. Ethinyl estradiol bioavailability is approximately 43 percent due to small-intestinal and hepatic first-pass metabolism.

Table 3.Mean ±SD Pharmacokinetic Parameters Following Single Dose Administration of WYMZYA Fe in Healthy Female Subjects Under Fasting Conditions.
Norethindrone/Ethinyl Estradiol | tmax (h) | Cmax (pg/mL) | AUC0 to ∞ (pg•h/mL) | t1/2 (h)
Norethindrone 0.4 mg | 1.24 ± 0.40 [n = 26] | 4210.6 ± 1628.8 | 18034.9 ± 7852.9 [n = 25] | 8.6 ± 3.7
Ethinyl Estradiol 35 mcg | 1.44 ± 0.33 | 131.4 ± 34.2 | 1065.8 ± 276.2 | 17.1 ± 4.4

Cmax = maximum plasma concentration; tmax = time to reach Cmax; AUC = area under the curve;

t1/2 = elimination half- life.

Food Effect:

Single-dose administration of WYMZYA Fe tablets with food decreased the maximum norethindrone and ethinyl estradiol concentration by 53 percent and 47 percent, respectively; the extent of norethindrone and ethinyl estradiol absorption (AUC values) was not affected by food administration.

Distribution

Norethindrone is 36 percent bound to sex hormone-binding globulin (SHBG) and 61 percent bound to albumin. Ethinyl estradiol is not bound to SHBG but is highly (98.5 percent) bound to albumin. Volume of distribution of norethindrone and ethinyl estradiol ranges from 2 to 4 L/kg.

Metabolism

Norethindrone undergoes extensive biotransformation, primarily via reduction, followed by sulfate and glucuronide conjugation; less than 5 percent of a norethindrone dose is excreted unchanged; greater than 50 percent and 20 to 40 percent of a dose is excreted in urine and feces, respectively. The majority of metabolites in the circulation are sulfates, with glucuronides accounting for most of the urinary metabolites.

Ethinyl estradiol is also extensively metabolized, both by oxidation and by conjugation with sulfate and glucuronide. Sulfates are the major circulating conjugates of ethinyl estradiol, and glucuronides predominate in urine. The primary oxidative metabolite is 2-hydroxy-ethinyl estradiol, which is formed by the CYP3A4 isoform of cytochrome P450.

Excretion

Plasma clearance values for norethindrone and ethinyl estradiol are similar (approximately 0.4 L/hr/kg). Ethinyl estradiol and norethindrone are excreted in both urine and feces, primarily as metabolites. Ethinyl estradiol is excreted in urine and feces as glucuronides and sulfates, and about 28 to 43 percent undergoes enterohepatic circulation. The mean terminal elimination half- lives of norethindrone and ethinyl estradiol following single dose administration of WYMZYA Fe are approximately 9 hours and 17 hours, respectively.

13 NONCLINICAL TOXICOLOGY

13.1 Carcinogenesis, Mutagenesis, Impairment of Fertility

[See WARNINGS AND PRECAUTIONS (5.11) and USE IN SPECIFIC POPULATIONS (8.1)].

14 CLINICAL STUDIES

The data presented in Section 14 are from a clinical trial conducted with norethindrone 0.4 mg/ethinyl estradiol 35 mcg tablets. WYMZYA Fe is bioequivalent to these norethindrone acetate/ethinyl estradiol tablets.

In a multicenter open-label clinical trial, 1,970 women, 98% of whom were 16 to 39 years of age, were studied for up to 31 cycles (28 days per cycle) to assess the efficacy of norethindrone /ethinyl estradiol tablets, completing the equivalent of 20,230 cycles of exposure. The racial demographic of all enrolled women was: Caucasian (56%), African-American (14%), and Other (30%) (Hispanic, Native American, etc.). Of treated women, 10% were lost to follow-up, 11% discontinued related to cycle control and 7% discontinued due to other adverse events

The pregnancy rate (Pearl Index [PI]) in all 1,970 women was 1.48 pregnancies per 100 women- years of use (95% confidence interval 0.94 –2.22), based on 23 pregnancies that occurred after the onset of treatment of norethindrone /ethinyl estradiol tablets.

16 HOW SUPPLIED/STORAGE AND HANDLING

16.1 How Supplied

WYMZYA Fe [norethindrone and ethinyl estradiol tablets USP (chewable) and ferrous fumarate tablets] is available in a blister pack (NDC 68180-873-71) containing 28 tablets packed in a pouch (NDC 68180-873-71). Such three pouches are packaged in a carton (NDC 68180-873-73).

Each blister contains 28 tablets in the following order:

- 21 white to off-white, round (active), flat face, beveled edge tablets debossed with "LU" on one side and "M21" on the other side and each containing 0.4 mg norethindrone and 35 mcg ethinyl estradiol.
- 7 brown, mottled, round (non-hormonal placebo), flat face, beveled edge tablets debossed with "LU" on one side and "M22" on the other side and each containing 75 mg ferrous fumarate.

16.2 Storage Conditions

- Store at 25°C (77°F); excursions permitted to 15 to 30°C (59 to 86°F) [see USP Controlled Room Temperature].
- Keep this and all medications out of the reach of children.

17 PATIENT COUNSELING INFORMATION

See FDA-Approved Patient Labeling (Patient Information and Instructions for Use)

Counsel patients about the following information:

- Cigarette smoking increases the risk of serious cardiovascular events from COC use, and that women who are over 35 years old and smoke should not use COCs [see BOXED WARNING].
- Increased risk of VTE compared to non-users of COCs is greatest after initially starting a COC or restarting (following a 4-week or greater pill-free interval) the same or a different COC [see WARNINGS AND PRECAUTIONS (5.1)] .
- WYMZYA Fe does not protect against HIV infection (AIDS) and other sexually transmitted diseases.
- WYMZYA Fe is not to be used during pregnancy; if pregnancy occurs during use of WYMZYA Fe, instruct the patient to stop further use [see WARNINGS AND PRECAUTIONS (5.9)].
- Take one tablet daily by mouth at the same time every day. Instruct patients what to do in the event pills are missed [see DOSAGE AND ADMINISTRATION (2.3)].
- Use a back-up or alternative method of contraception when enzyme inducers are used with WYMZYA Fe [see DRUG INTERACTIONS (7.1)].
- COCs may reduce breast milk production; this is less likely to occur if breastfeeding is well established [see USE IN SPECIFIC POPULATIONS (8.3)].
- A woman who starts COCs postpartum and who has not yet had a period should use an additional method of contraception until she has taken a white tablet for 7 consecutive days [see DOSAGE AND ADMINISTRATION (2.2)].
- Amenorrhea may occur. Consider pregnancy in the event of amenorrhea at the time of the first missed period. Rule out pregnancy in the event of amenorrhea in two or more consecutive cycles [see WARNINGS AND PRECAUTIONS (5.8)].

Distributed by:

Lupin Pharmaceuticals, Inc.

Naples, FL 34108

United States

Manufactured by:

Lupin Limited

Pithampur (M.P.) - 454 775

India

Revised: November 2024

Patient Information

WYMZYATM Fe

[WYM-zee-yah EFF-EE]

[norethindrone and ethinyl estradiol tablets (chewable) and ferrous fumarate tablets]

What is the most important information I should know about WYMZYA Fe?

Do not use WYMZYA Fe if you smoke cigarettes and are over 35 years old. Smoking increases your risk of serious cardiovascular side effects (heart and blood vessel problems) from birth control pills, including death from heart attack, blood clots or stroke. This risk increases with age and the number of cigarettes you smoke.

What is WYMZYA Fe?

WYMZYA Fe is a birth control pill (oral contraceptive) used by women to prevent pregnancy.

How does WYMZYA Fe work for contraception?

Your chance of getting pregnant depends on how well you follow the directions for taking your birth control pills. The better you follow the directions, the less chance you have of getting pregnant.

Based on the results of one clinical study of a 28-day regimen of norethindrone 0.4 mg/ethinyl estradiol 35 mcg tablets, about 1 to 2 out of 100 women may get pregnant during the first year they use WYMZYA Fe.

The following chart shows the chance of getting pregnant for women who use different methods of birth control. Each box on the chart contains a list of birth control methods that are similar in effectiveness. The most effective methods are at the top of the chart. The box on the bottom of the chart shows the chance of getting pregnant for women who do not use birth control and are trying to get pregnant.

Who should not take WYMZYA Fe?

Do not take WYMZYA Fe if you:

- smoke and are over 35 years of age
- had blood clots in your arms, legs, lungs, or eyes
- had a problem with your blood that makes it clot more than normal
- have certain heart valve problems or irregular heart beat that increases your risk of having blood clots
- had a stroke
- had a heart attack
- have high blood pressure that cannot be controlled by medicine
- have diabetes with kidney, eye, nerve, or blood vessel damage
- have certain kinds of severe migraine headaches with aura, numbness, weakness or changes in vision, or any migraine headaches if you are over 35 years of age
- have liver problems, including liver tumors
- have any unexplained vaginal bleeding
- are pregnant
- had breast cancer or any cancer that is sensitive to female hormones
- Take any Hepatitis C drug combination containing ombitasvir/paritaprevir/ritonavir, with or without dasabuvir. This may increase levels of the liver enzyme "alanine aminotransferase" (ALT) in the blood.

If any of these conditions happen while you are taking WYMZYA Fe , stop taking WYMZYA Fe right away and talk to your healthcare provider. Use non-hormonal contraception when you stop taking WYMZYA Fe.

What should I tell my healthcare provider before taking WYMZYA Fe?

Tell your healthcare provider if you:

- are pregnant or think you may be pregnant
- are depressed now or have been depressed in the past
- had yellowing of your skin or eyes (jaundice) caused by pregnancy (cholestasis of pregnancy)
- are breastfeeding or plan to breastfeed. WYMZYA Fe may decrease the amount of breast milk you make. A small amount of the hormones in WYMZYA Fe may pass into your breast milk. Talk to your healthcare provider about the best birth control method for you while breastfeeding.

Tell your healthcare provider about all the medicines you take, including prescription and over-the-counter medicines, vitamins and herbal supplements.

WYMZYA Fe may affect the way other medicines work, and other medicines may affect how well WYMZYA Fe works.

Know the medicines you take. Keep a list of them to show your healthcare provider and pharmacist when you get a new medicine.

How do I take WYMZYA Fe?

Read the Instructions for Use at the end of this Patient Information.

What are the possible serious side effects of WYMZYA Fe?

- Like pregnancy, WYMZYA Fe may cause serious side effects, including blood clots in your lungs, heart attack, or a stroke that may lead to death . Some other examples of serious blood clots include blood clots in the legs or eyes.

Serious blood clots can happen especially if you smoke, are obese, or are older than 35 years of age. Serious blood clots are more likely to happen when you:

- first start taking birth control pills
- restart the same or different birth control pills after not using them for a month or more

Call your healthcare provider or go to a hospital emergency room right away if you have:

- leg pain that will not go away
- sudden severe shortness of breath
- sudden change in vision or blindness
- chest pain
- a sudden, severe headache unlike your usual headaches
- weakness or numbness in your arm or leg
- trouble speaking

Other serious side effects include:

- liver problems, including:
  - rare liver tumors
  - jaundice (cholestasis), especially if you previously had cholestasis of pregnancy. Call your healthcare provider if you have yellowing of your skin or eyes.
- high blood pressure . You should see your healthcare provider for a yearly check of your blood pressure.
- gallbladder problems
- changes in the sugar and fat (cholesterol and triglycerides) levels in your blood
- new or worsening headaches including migraine headaches
- depression
- possible cancer in your breast and cervix
- swelling of your skin especially around your mouth, eyes, and in your throat (angioedema) . Call your healthcare provider if you have a swollen face, lips, mouth tongue or throat, which may lead to difficulty swallowing or breathing. Your chance of having angioedema is higher if you have a history of angioedema.
- dark patches of skin around your forehead, nose, cheeks and around your mouth, especially during pregnancy (chloasma). Women who tend to get chloasma should avoid spending a long time in sunlight, tanning booths, and under sun lamps while taking WYMZYA Fe. Use sunscreen if you have to be in the sunlight.

What are the most common side effects of WYMZYA Fe?

The most common side effects of WYMZYA Fe include:

- headache (including migraine)
- nausea and vomiting
- breast problems
  - tenderness, pain and discomfort
  - enlargement and swelling
  - discharge
  - nipple pain
- belly pain
- pain with your periods (menstrual cycle)
- mood changes, including depression
- acne
- vaginal infections
- bloating
- weight gain

These are not all the possible side effects of WYMZYA Fe . For more information, ask your healthcare provider or pharmacist.

You may report side effects to the FDA at 1-800-FDA-1088.

What else should I know about taking WYMZYA Fe?

- If you are scheduled for any lab tests, tell your healthcare provider you are taking WYMZYA Fe. Certain blood tests may be affected by WYMZYA Fe.
- WYMZYA Fe does not protect against HIV infection (AIDS) and other sexually transmitted infections.

How should I store WYMZYA Fe?

- Store WYMZYA Fe at room temperature between 68°F to 77°F (20°C to 25°C).
- Keep WYMZYA Fe and all medicines out of the reach of children.
- Store away from light.

General information about the safe and effective use of WYMZYA Fe.

Medicines are sometimes prescribed for purposes other than those listed in a Patient Information leaflet. Do not use WYMZYA Fe for a condition for which it was not prescribed. Do not give WYMZYA Fe to other people.

This Patient Information summarizes the most important information about WYMZYA Fe. You can ask your pharmacist or healthcare provider for information about WYMZYA Fe that is written for health professionals.

For more information, call Lupin Pharmaceuticals, Inc. at 1-800-399-2561.

Does hormonal birth control cause cancer?

It is not known if hormonal birth control pills causes breast cancer. Some studies, but not all, suggest that there could be a slight increase in the risk of breast cancer among current users with longer duration of use.

If you have breast cancer now, or have had it in the past, do not use hormonal birth control because some breast cancers are sensitive to hormones.

Women who use birth control pills may have a slightly higher chance of getting cervical cancer. However, this may be due to other reasons such as having more sexual partners.

What if I want to become pregnant?

You may stop taking the pill whenever you wish. Consider a visit with your healthcare provider for a pre-pregnancy checkup before you stop taking the pill.

What should I know about my period when taking WYMZYA Fe?

Your periods may be lighter and shorter than usual. Some women may miss a period. Irregular vaginal bleeding or spotting may happen while you are taking WYMZYA Fe, especially during the first few months of use. This usually is not a serious problem. It is important to continue taking your pills on a regular schedule to prevent a pregnancy.

What are the ingredients in WYMZYA Fe?

Active ingredients:

White pills: norethindrone and ethinyl estradiol

Brown pills: ferrous fumarate

Inactive ingredients:

White pills: lactose anhydrous, magnesium stearate, mannitol, microcrystalline cellulose, povidone, sodium starch glycolate, sucralose, vanillin and vitamin E.

Brown pills: magnesium stearate, microcrystalline cellulose, povidone, sodium starch glycolate and sucrose.

Instructions For Use

WYMZYATM Fe

[WYM-zee-yah EFF-EE]

[norethindrone and ethinyl estradiol tablets (chewable) and ferrous fumarate tablets]

Important Information about taking WYMZYA Fe

- Take 1 pill every day at the same time. Take the pills in the order directed on your replace.
- Both the white pills and the brown pills may be swallowed whole or chewed and swallowed. If the pill is chewed, drink a full glass (8 ounces) of liquid immediately after swallowing.
- Do not skip your pills, even if you do not have sex often. If you miss pills (including starting the pack late) you could get pregnant . The more pills you miss, the more likely you are to get pregnant.
- If you have trouble remembering to take WYMZYA Fe, talk to your healthcare provider. When you first start taking WYMZYA Fe, spotting or light bleeding in between your periods may occur. Contact your healthcare provider if this does not go away after a few months.
- You may feel sick to your stomach (nauseous), especially during the first few months of taking WYMZYA Fe. If you feel sick to your stomach, do not stop taking the pill. The problem will usually go away. If your nausea does not go away, call your healthcare provider.
- Missing pills can also cause spotting or light bleeding, even when you take the missed pills later. On the days you take 2 pills to make up for missed pills (see below), you could also feel a little sick to your stomach.
- It is not uncommon to miss a period. However, if you miss a period and have not taken WYMZYA Fe according to directions, or miss 2 periods in a row, or feel like you may be pregnant, call your healthcare provider. If you have a positive pregnancy test, you should stop taking WYMZYA Fe.
- If you have vomiting or diarrhea within 3 to 4 hours of taking your pill, take another pill of the same color from your extra replace. If you do not have an extra replace, take the next pill in your replace. Continue taking all your remaining pills in order. Start the first pill of your next replace the day after finishing your current replace. This will be 1 day earlier than originally scheduled. Continue on your new schedule.
- If you have vomiting or diarrhea for more than 1 day, your birth control pills may not work as well. Use an additional birth control method, like condoms and a spermicide, until you check with your healthcare provider.
- Stop taking WYMZYA Fe at least 4 weeks before you have major surgery and do not restart after the surgery without asking your healthcare provider. Be sure to use other forms of contraception (like condoms and spermicide) during this time period.

Before you start taking WYMZYA Fe:

- Decide what time of day you want to take your pill. It is important to take it at the same time every day and in the order as directed on your blister.
- Have backup contraception (condoms and spermicide) available and if possible, an extra full pack of pills as needed.

When should I start taking WYMZYA Fe?

If you start taking WYMZYA Fe and you have not used a hormonal birth control method before:

- There are 2 ways to start taking your birth control pills. You can either start on a Sunday (Sunday Start) or on the first day (Day 1) of your natural menstrual period (Day 1 Start). Your healthcare provider should tell you when to start taking your birth control pill.
- If you use the Sunday Start, use non-hormonal back-up contraception such as condoms and spermicide for the first 7 days that you take WYMZYA Fe. You do not need back-up contraception if you use the Day 1 Start.

If you start taking WYMZYA Fe and you are switching from another birth control pill:

- Start your new WYMZYA Fe pack on the same day that you would start the next pack of your previous birth control method.
- Do not continue taking the pills from your previous birth control pack.

If you start taking WYMZYA Fe and previously used a vaginal ring or transdermal patch:

- Start using WYMZYA Fe on the day you would have reapplied the next ring or patch.

If you start taking WYMZYA Fe and you are switching from a progestin-only method such as an implant or injection:

- Start taking WYMZYA Fe on the day of removal of your implant or on the day when you would have had your next injection.

If you start taking WYMZYA Fe and you are switching from an intrauterine device or system (IUD or IUS):

- Start taking WYMZYA Fe on the day of removal of your IUD or IUS.
- You do not need back-up contraception if your IUD or IUS is removed on the first day (Day 1) of your period. If your IUD or IUS is removed on any other day, use non-hormonal back-up contraception such as condoms and spermicide for the first 7 days that you take WYMZYA Fe.

Keep a calendar to track your period:

If this is the first time you are taking birth control pills, read, "When should I start taking WYMZYA Fe?" above. Follow these instructions for either a Sunday Start or a Day 1 Start.

Sunday Start:

You will use a Sunday Start if your healthcare provider told you to take your first pill on a Sunday.

- Take pill 1 on the Sunday after your period starts .
- If your period starts on a Sunday, take pill "1 " that day and refer to Day 1 Start instructions below.
- Take 1 pill every day in the order on the blister at the same time each day for 28 days.
- After taking the last pill on Day 28 from the blister, start taking the first pill from a new pack, on the same day of the week as the first pack (Sunday). Take the first pill in the new pack whether or not you are having your period.
- Use non-hormonal back-up contraception such as condoms and spermicide for the first 7 days of the first cycle that you take WYMZYA Fe.

Day 1 Start:

You will use a Day 1 Start if your doctor told you to take your first pill (Day 1) on the first day of your period.

- Take 1 pill every day in the order of the blister, at the same time each day, for 28 days.
- After taking the last pill on Day 28 from the blister, start taking the first pill from a new pack, on the same day of the week as the first pack. Take the first pill in the new pack whether or not you are having your period.

Instructions for using your blister (pill pack):

Step 1.

Look at your WYMZYA Fe pill pack. See Figure A.

The WYMZYA Fe pill pack has:

- 21 white (active) pills with hormone for Week 1 through Week 3 .
- 7 brown (inactive) pills without hormones for Week 4 .

Step 2.

Find:

- where on your pack to start taking pills
- in what order to take your pills (follow the arrows)
- the week numbers

Step 3.

Remove the white pill by pressing the pill through the foil in the bottom of the pill pack. Continue taking the white pills for 21 days.

Step 4.

On the first day of Week 4 start taking the brown pills. Take the brown pill for 7 days.Your period should start during this time.

Step 5.

When you have taken all of the brown pills in your pill pack, get a new pill pack and start taking the white pills.

- For a Day 1 start:

Begin your next pill pack on the same day of the week as your first cycle pill pack.

- For a Sunday Start:

Begin your next pill pack on Sunday.

What should I do if I miss any WYMZYA Fe pills?

If you miss 1 pill in Weeks 1, 2, or 3, follow these steps:

- Take it as soon as you remember. Take the next pill at your regular time. This means you may take 2 pills in 1 day.
- Then continue taking 1 pill every day until you finish the pack.
- You do not need to use a back-up birth control method if you have sex.

If you miss 2 pills in Week 1 or Week 2 of your pack, follow these steps:

- Take the 2 missed pills as soon as possible and the next 2 pills the next day.
- Then continue to take1 pill every day until you finish the pack.
- Use a non-hormonal birth control method (such as a condom and spermicide) as a back-up if you have sex during the first 7 days after missing your pills.

If you miss 2 pills in a row in Week 3, or you miss 3 or more pills in a row during Weeks 1, 2, or 3 of the pack, follow these steps:

- If you are a Day 1 Starter:
  - Throw out the rest of the pill pack and start a new pack that same day.
- If you are a Sunday Starter:
  - Keep taking 1 pill every day until Sunday. On Sunday, throw out the rest of the pack and start a new pack of pills that same day.
- You may not have your period this month but this is expected. However, if you miss your period 2 months in a row, call your healthcare provider because you might be pregnant.
- You could become pregnant if you have sex during the first 7 days after you restart your pills. You MUST use a non-hormonal birth control method (such as a condom and spermicide) as a back-up if you have sex during the first 7 days after you restart your pills.

If you have any questions or are unsure about the information in this leaflet, call your healthcare provider.

This Patient Information and Instructions for Use has been approved by the U.S. Food and Drug Administration.

WYMZYA™ Fe is a trademark of Lupin Pharmaceuticals, Inc.

Distributed by:

Lupin Pharmaceuticals, Inc.

Naples, FL 34108

United States

Manufactured by:

Lupin Limited

Pithampur (M.P.) - 454 775

India

Revised: November 2024 ID#: 277223

PACKAGE LABEL

WYMZYATM Fe [norethindrone and ethinyl estradiol tablets USP (chewable), 0.4 mg/0.035 mg and ferrous fumarate tablets, 75 mg]

Rx only

NDC 68180-873-71

Blister Label: 28 Tablets

WYMZYATM Fe [norethindrone and ethinyl estradiol tablets USP (chewable), 0.4 mg/0.035 mg and ferrous fumarate tablets, 75 mg]

Rx only

NDC 68180-873-71

Pouch Label: 1 blister of 28 Tablets

WYMZYATM Fe [norethindrone and ethinyl estradiol tablets USP (chewable), 0.4 mg/0.035 mg and ferrous fumarate tablets, 75 mg]

Rx only

NDC 68180-873-73

Carton Label: 3 blisters of 28 Tablets